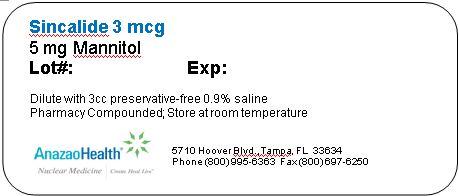 DRUG LABEL: SIncalide
NDC: 51808-203 | Form: INJECTION, POWDER, LYOPHILIZED, FOR SOLUTION
Manufacturer: AnazaoHealth Corporation
Category: prescription | Type: HUMAN PRESCRIPTION DRUG LABEL
Date: 20120619

ACTIVE INGREDIENTS: SINCALIDE 3 ug/1 1
INACTIVE INGREDIENTS: MANNITOL 5 mg/1 1

Sincalide

Dear Medical Professional,

Per your order, we have compounded Sincalide as a sterile lyophilized powder, sealed under nitrogen. The characteristics of this compounded preparation are as follows

DESCRIPTION

- Upon reconstitution with 3 ml normal saline, the vial contains
  - 1 mcg/ml Sincalide
  - 5 mg Mannitol
- Lyophilized product should be stored at room temperature. After reconstitution with normal saline, the vial can be stored in the refrigerator for use within 12 hours.

Normal dosing is 0.02 micrograms per kilogram patient weight. A 70 kg patient would receive 1.4 mcg or 1.4 ml

CLINICAL PHARMACOLOGY

Sincalide, a synthetically prepared C-terminal octapeptide of the natural hormone cholecystokinin, induces contraction of the gallbladder muscle, resulting in reduction of gallbladder size and evacuation of bile. Also, Sincalide, like cholecystokinin, stimulates secretion of pancreatic enzymes;Sincalide decreases intestinal transit time; delays gastric emptying; decreases esophageal sphincter tone; inhibits gastric secretions; and stimulates intestinal muscle. Maximum contraction (40% reduction in size) of gallbladder occurs 5 to 15 minutes after injection. Gallbladder returns to basal size within 1 hour

INDICATIONS AND USAGE

Sincalide may be used: to stimulate gallbladder contraction, as may be assessed by various methods of diagnostic imaging, or to obtain by duodenal aspiration a sample of concentrated bile for analysis of cholesterol, bile salts, phospholipids, and crystals; to stimulate pancreatic secretion (especially in conjunction with secretin) prior to obtaining a duodenal aspirate for analysis of enzyme activity, composition, and cytology; to accelerate the transit of a barium meal through the small bowel, thereby decreasing the time and extent of radiation associated with fluoroscopy and x-ray examination of the intestinal tract

CONTRAINDICATIONS

Gallbladder stones (stimulation of gallbladder contraction in patients with small gallbladder stones may lead to the evacuation of the stones from the gallbladder resulting in their lodging in the cystic duct or in the common bile duct; however, this is unlikely with usual doses of Sincalide since complete contraction of the gallbladder is not induced.)

ADVERSE REACTIONS

The following side/adverse effects have been selected on the basis of their potential clinical significance (possible signs and symptoms in parentheses where appropriate) – not necessarily inclusive:

- Those indicating need for medical attention with an Incidence that is less frequent or rare include allergic reaction (shortness of breath, skin rash) , hypotension (dizziness, lightheadedness, or fainting) or Increase in blood pressure
- More frequent adverse reaction include Gastrointestinal effects (nausea, abdominal or stomach pain, cramps, or discomfort) – 20% incidence, diarrhea, dizziness , flushing or redness of skin , headache , increased sweating , numbness , sneezing , urge to have bowel movement or vomiting

Note: The less frequent side effects listed occur in less than 1% of patients, except for diarrhea, which occurs in about 2% of patients. The above side effects are generally mild and of short duration; they are usually lessened by a slower injection rate

DOSAGE AND ADMINISTRATION

To reconstitute, aseptically add 3 mL of preservative free 0.9% sodium chloride to the vial and swirl. This solution may be kept at room temperature and should be used within 8 hours of reconstitution, after which time any unused portion should be discarded.

The vial should be inspected visually for particulate matter and discoloration prior to administration.

For prompt contraction of the gallbladder, a dose of 0.02 mcg sincalide per kg (1.4 mcg/70 kg) is injected intravenously over a 30- to 60-second interval; if satisfactory contraction of the gallbladder does not occur in 15 minutes, a second dose, 0.04 mcg sincalide per kg, may be administered. To reduce the intestinal side effects, an intravenous infusion may be prepared at a dose of 0.12 mcg/kg in 100 mL of Sodium Chloride Injection USP and given at a rate of 2 mL per minute; alternatively, an intramuscular dose of 0.1 mcg/kg may be given.

To accelerate the transit time of a barium meal through the small bowel, administer Sincalide after the barium meal is beyond the proximal jejunum. (Sincalide, like cholecystokinin, may cause pyloric contraction.) The recommended dose is 0.04 mcg sincalide per kg (2.8 mcg/70 kg) injected intravenously over a 30- to 60- second interval; if satisfactory transit of the barium meal has not occurred in 30 minutes, a second dose of 0.04 mcg sincalide per kg may be administered. For reduction of side effects, a 30-minute IV infusion of sincalide [0.12 mcg per kg (8.4 mcg/70 kg) diluted to approximately 100 mL with Sodium Chloride Injection USP] may be administered

Storage and Handling

The preparation should be stored at room temperature